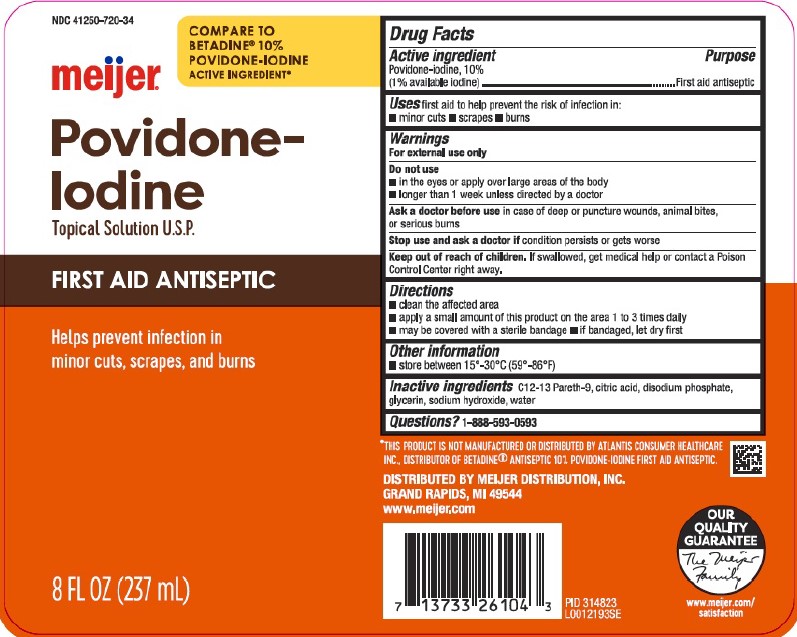 DRUG LABEL: First Aid Antiseptic
NDC: 41250-720 | Form: SOLUTION
Manufacturer: Meijer, Inc.
Category: otc | Type: HUMAN OTC DRUG LABEL
Date: 20260219

ACTIVE INGREDIENTS: POVIDONE-IODINE 10 mg/1 mL
INACTIVE INGREDIENTS: C12-13 PARETH-9; CITRIC ACID MONOHYDRATE; SODIUM PHOSPHATE, DIBASIC, ANHYDROUS; GLYCERIN; SODIUM HYDROXIDE; WATER

Meijer 050.002/050AE
Povidone-Iodine Solution, 10%

Active ingredient

Povidone-iodine, 10% (1% available iodine)

purpose

First aid antiseptic

Uses

first aid to help prevent the risk of infection in:

- minor cuts
- scrapes
- burns

Warnings

For external use only

Do not use

- in the eyes or aply over large areas of the body
- longer than 1 week unless directed by a doctor

Ask a doctor before use

in case of deep or puncture wounds, animal bites, or serious burns

Stop use and ask a doctor if

condition persists or gets worse

Keep out of reach of children.

If swallowed, get medical help or contact a Poison Control Center right away.

Directions

- clean the affected area
- apply a small amount of this product on the area 1 to 3 times daily
- may be covered with a sterile bandage
- if bandaged, let dry first

Other information

- store between 15°-30°C (59°-86°F)

Inactive ingredients

C12-13 Pareth-9, citric acid, disodium phosphate, glycerin, sodium hydroxide, water

Questions?

1-888-593-0593

Disclaimer

*THIS PRODUCT IS NOT MANUFACTURED OR DISTRIBUTED BY ATLANTIS CONSUMER HEALTHCARE INC., DISTRIBUTOR OF BETADINEANTISEPTIC 10% POVIDONE-IODINE FIRST AID ANTISEPTIC.

Adverse Reaction

DISTRIBUTED BY MEIJER DISTRIBUTION, INC.

GRAND RAPIDS, MI 49544

www.meijer.com

OUR QUALITY GUARANTEE

The Meijer Family

www.meijer.com/satisfaction

PID 314823

Principal display panel

NDC 41250-720-34

COMPARE TO BETADINE®10% POVIDONE-IODINE ACTIVE INGREDIENT*

meijer®

Povidone-Iodine

Topical Solution U.S.P.

FIRST AID ANTISEPTIC

Helps Prevent Infection in minor cuts, scrapes, and burns

8 FL OZ (237 mL)